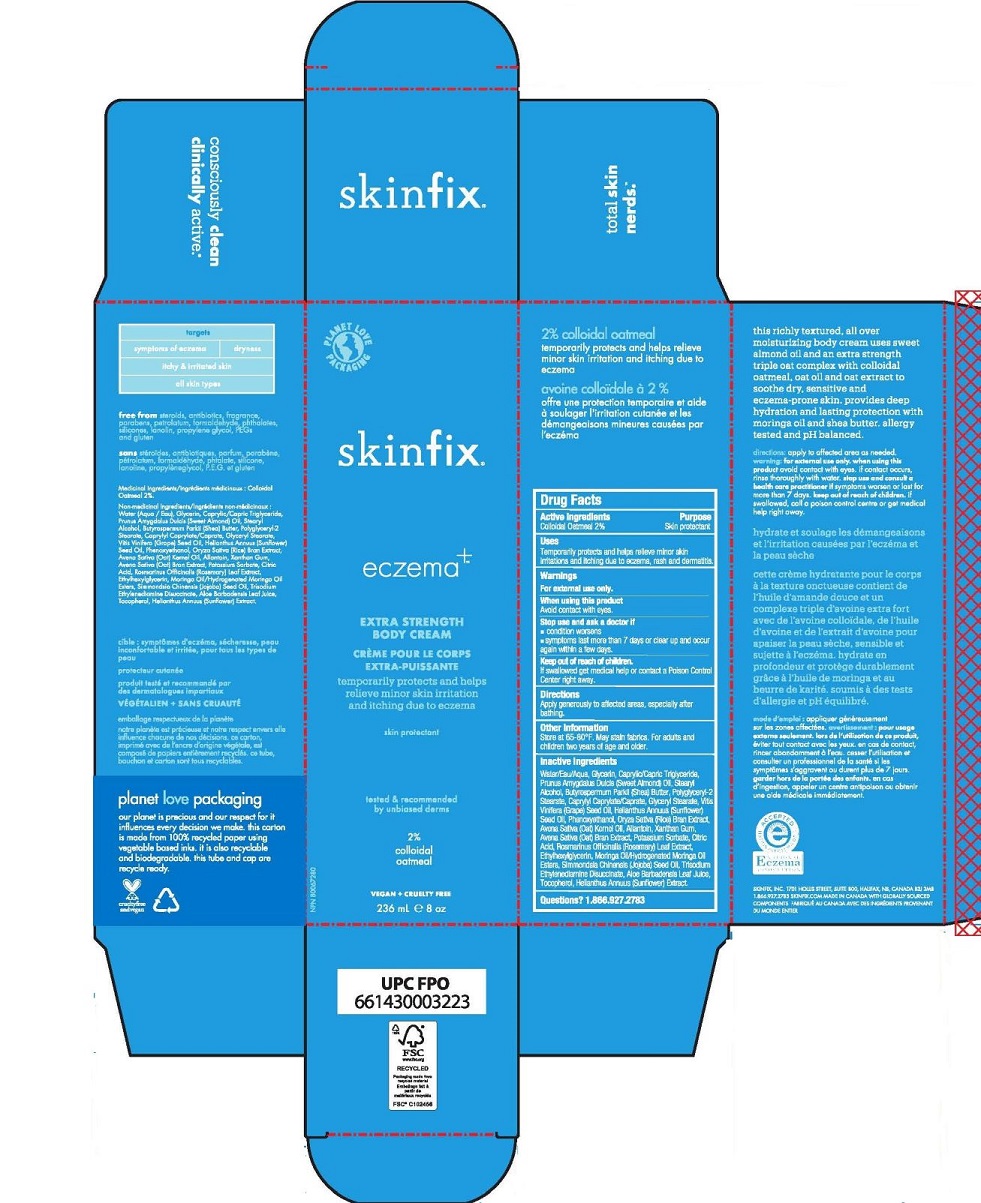 DRUG LABEL: EXTRA STRENGTH BODY
NDC: 61328-119 | Form: CREAM
Manufacturer: Skinfix, Inc.
Category: otc | Type: HUMAN OTC DRUG LABEL
Date: 20251229

ACTIVE INGREDIENTS: OATMEAL 2 g/100 mL
INACTIVE INGREDIENTS: ALLANTOIN; ALOE VERA LEAF; AVENA SATIVA WHOLE; OAT KERNEL OIL; SHEA BUTTER; MEDIUM-CHAIN TRIGLYCERIDES; CAPRYLYL CAPRYLATE/CAPRATE; ANHYDROUS CITRIC ACID; ETHYLHEXYLGLYCERIN; GLYCERIN; GLYCERYL MONOSTEARATE; SUNFLOWER OIL; HELIANTHUS ANNUUS WHOLE; MORINGA OLEIFERA SEED OIL; RICE BRAN; PHENOXYETHANOL; POLYGLYCERYL-2 STEARATE; POTASSIUM SORBATE; ALMOND OIL; ROSEMARY; JOJOBA OIL; STEARYL ALCOHOL; TOCOPHEROL; TRISODIUM ETHYLENEDIAMINE DISUCCINATE; GRAPE SEED OIL; WATER; XANTHAN GUM

EXTRA STRENGTH BODY

Active Ingredients

Colloidal Oatmeal 2%

Purpose

Skin protectant

Uses

Temporarily protects and helps relieve minor skin irritations and itching due to eczema rash and dermatitis.

Warnings

For external use only.

When using this product, avoid contact with eyes.

Stop use and ask a doctor if

- condition worsens
- symptoms last more than 7 days or clear up and occur again within a few days.

When using this product

- Avoid contact with eyes

Stop use and ask a doctor if

- condition worsens
- symptoms last more than 7 days or clear up and occur again within a few days

Keep out of reach of children. If swallowed get medical help or contact a Poison Control Center right away.

Directions

Apply generously to affected areas, especially after bathing.

Inactive Ingredients

Water/Eau/Aqua, Glycerin, Caprylic/Capric Triglyceride, Prunus Amygdalus Dulcis (Sweet Almond) Oil, Stearyl Alcohol, Butyrospermum Parkii (Shea) Butter, Polyglyceryl-2 Stearate, Caprylyl Caprylate/Caprate, Glyceryl Stearate, Vitis Vinifera (Grape) Seed Oil, Helianthus Annuus (Sunflower) Seed Oil, Phenoxyethanol, Oryza Sativa (Rice) Bran Extract, Avena Sativa (Oat) Kernel Oil, Allantoin, Xanthan Gum, Avena Sativa (Oat) Bran Extract, Potassium Sorbate, Citric Acid, Rosmarinus Officinalis (Rosemary) Leaf Extract, Ethylhexylglycerin, Moringa Oil/Hydrogenated Moringa Oil Esters, Simmondsia Chinensis (Jojoba) Seed Oil, Trisodium Ethylenediamine Disuccinate, Aloe Barbadensis Leaf Juice, Tocopherol, Helianthus Annuus (Sunflower) Extract.